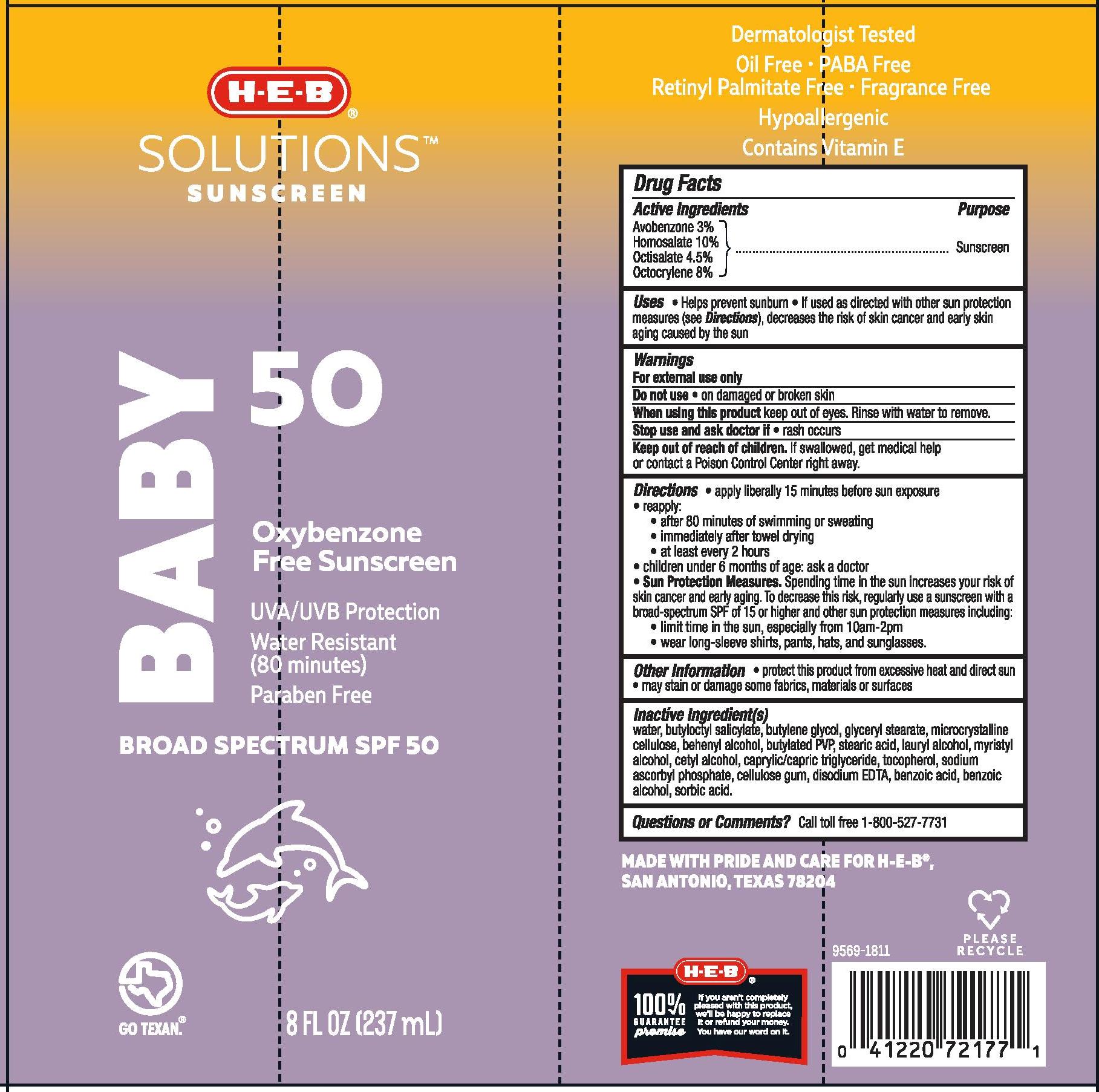 DRUG LABEL: H.E.B BABY
NDC: 37808-913 | Form: AEROSOL, SPRAY
Manufacturer: H.E.B
Category: otc | Type: HUMAN OTC DRUG LABEL
Date: 20241015

ACTIVE INGREDIENTS: AVOBENZONE 30 mg/1 mL; HOMOSALATE 100 mg/1 mL; OCTISALATE 45 mg/1 mL; OCTOCRYLENE 80 mg/1 mL
INACTIVE INGREDIENTS: WATER; DOCOSANOL; GLYCERYL MONOSTEARATE; MICROCRYSTALLINE CELLULOSE; MYRISTYL ALCOHOL; STEARIC ACID; SORBIC ACID; LAURYL ALCOHOL; CETYL ALCOHOL; SODIUM ASCORBYL PHOSPHATE; BENZOIC ACID; TOCOPHEROL; MEDIUM-CHAIN TRIGLYCERIDES; CARBOXYMETHYLCELLULOSE SODIUM; BUTYLOCTYL SALICYLATE; EDETATE DISODIUM; BUTYLENE GLYCOL

H-E-B SOLUTIONS SUNSCREEN BABY SPF 50 LOTION

Active Ingredients

Avobenzone 3.0%, Homosalate 10.0%, Octisalate 4.5%, Octocrylene 8.0%

Purpose

Sunscreen

Uses

- helps prevent sunburn
- if used as directed with other sun protetion measures (see Directions), decreases the risk of skin cancer and early skin aging caused by the sun

Warnings

For external use only

Do not use • on damaged or broken skin.

When using this product • keep out of eyes. Rinse with water to remove.

Stop use and ask a doctor if • rash occurs.

Keep out of reach of children. if swallowed, get medical help or contact a Poison Control Center right away.

Directions

- apply liberally 15 minutes before sun exposure
- reapply:

• after 80 minutes of swimming or sweating

• immediately after towel drying

• at least every 2 hours

- children under 6 months of age: ask a doctor
- Sun Protection Measures. Spending time in the sun increases your risk of skin cancer and early skin aging. To decrease this risk, regularly use a sunscreen with a broad-spectrum SPF of 15 or higher and other sun protection measures including:

• limit time in the sun, especially from 10 a.m. - 2 p.m.

• wear long-sleeve shirts, pants, hats, and sunglasses

Other Information

- protect this product from excessive heat and direct sun
- may stain or damage some fabrics, materials or surfaces

Inactive Ingredient(s)

water, butyloctyl salicylate, butylene glycol, glyceryl stearate, microcrystalline cellulose, behenyl alcohol, butylated PVP, stearic acid, lauryl alcohol, myristyl alcohol, cetyl alcohol, caprylic/capric triglyceride, tocopherol, sodium ascorbyl phosphate, cellulose gum, disodium EDTA, benzoic acid, benzoic alcohol, sorbic acid.

Questions or Comments?

Call toll free 1-800-527-7731

PACKAGE LABEL

H-E-B SOLUTIONS SUNSCREEN BABY SPF 50 LOTION

8 FL OZ (237mL)

NDC 37808-913-12